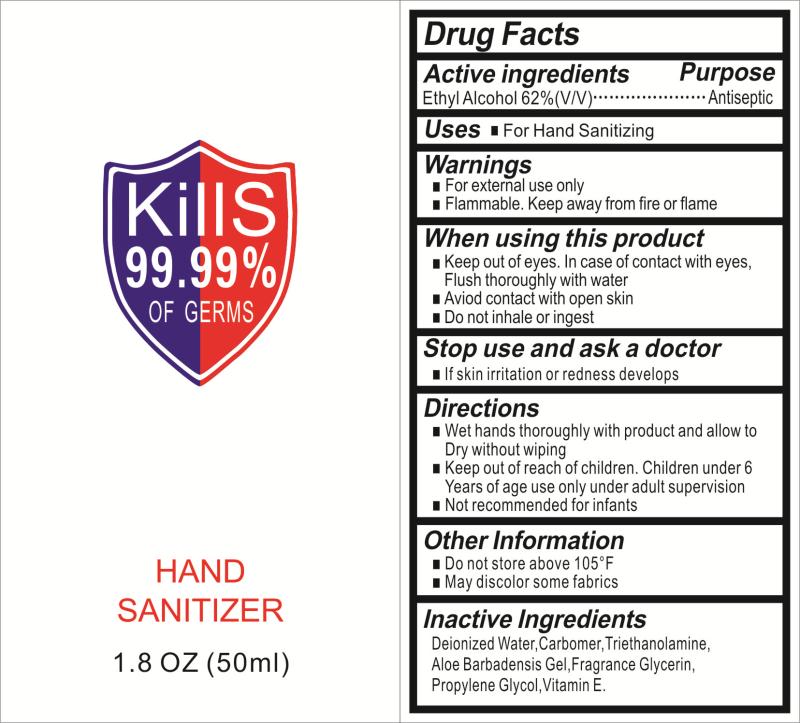 DRUG LABEL: Hand Sanitizer
NDC: 74746-001 | Form: GEL
Manufacturer: YUYAO WANGCHENG DAILY COMMODITY CO., LTD.
Category: otc | Type: HUMAN OTC DRUG LABEL
Date: 20200414

ACTIVE INGREDIENTS: ALCOHOL 62 mL/100 mL
INACTIVE INGREDIENTS: GLYCERIN; CARBOMER 934; WATER; PROPYLENE GLYCOL; TROLAMINE; ALOE VERA LEAF; ALPHA-TOCOPHEROL

74746-001 hand sanitizer

Active Ingredient(s)

Isopropyl Alcohol 62% v/v.

Purpose

Antiseptic

Use

For Hand Sanitizing

Warnings

■For external use only
■Flammable. Keep away from fire or flame
When using this product
1 Keep out of eyes. In case of contact with eyes,
Flush thoroughly with water
■Aviod contact with open skin
■Do not inhale or ingest
Stop use and ask a doctor
■If skin iritation or redness develops

Keep out of reach of children. Children under 6 Years of age use only under adult supervision
Not recommended for infants

Directions

■Wet hands thoroughly with product and allow to
Dry without wiping

Inactive ingredients

Deionized Water,Carbomer,Triethanolamine,
Aloe Barbadensis Gel,Fragrance Glycerin,
Propylene Glycol,Vitamin E.